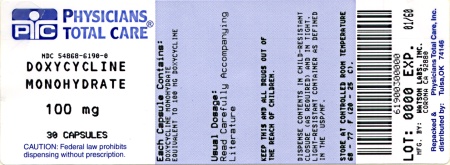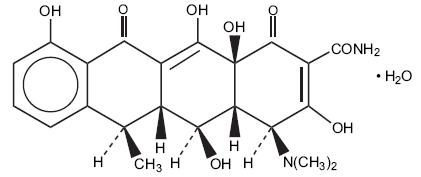 DRUG LABEL: Doxycycline Monohydrate
NDC: 54868-6190 | Form: CAPSULE
Manufacturer: Physicians Total Care, Inc.
Category: prescription | Type: HUMAN PRESCRIPTION DRUG LABEL
Date: 20120207

ACTIVE INGREDIENTS: DOXYCYCLINE 100 mg/1 1
INACTIVE INGREDIENTS: SILICON DIOXIDE; MAGNESIUM STEARATE; CELLULOSE, MICROCRYSTALLINE; SODIUM STARCH GLYCOLATE TYPE A POTATO; FERROSOFERRIC OXIDE; FERRIC OXIDE RED; TITANIUM DIOXIDE; FERRIC OXIDE YELLOW

Doxycycline Monohydrate Capsules
Revised: January 2012
Rx only
191157-4

To reduce the development of drug-resistant bacteria and maintain the effectiveness of Doxycycline Monohydrate Capsules and other antibacterial drugs, Doxycycline Monohydrate Capsules should be used only to treat or prevent infections that are proven or strongly suspected to be caused by bacteria.

DESCRIPTION

Doxycycline is a broad-spectrum antibiotic synthetically derived from oxytetracycline. Doxycycline Monohydrate Capsules 100 mg, 75 mg, and 50 mg contain doxycycline monohydrate equivalent to 100 mg, 75 mg, or 50 mg of doxycycline for oral administration. The chemical designation of the light-yellow crystalline powder is alpha-6-deoxy-5-oxytetracycline.

Structural formula:

C22H24N2O8 • H2O M.W. = 462.45

Doxycycline has a high degree of lipid solubility and a low affinity for calcium binding. It is highly stable in normal human serum. Doxycycline will not degrade into an epianhydro form.

Inert ingredients: colloidal silicon dioxide; magnesium stearate; microcrystalline cellulose; sodium starch glycolate; and a hard gelatin capsule which contains black iron oxide, red iron oxide, titanium dioxide, and yellow iron oxide for the 100 mg and 75 mg strengths, titanium dioxide and yellow iron oxide for the 50 mg strength. The capsules are printed with edible ink containing black iron oxide, red iron oxide, and yellow iron oxide for the 50 mg and 100 mg strengths and black iron oxide, FD&C Blue No. 2, FD&C Red No. 40, FD&C Blue No. 1, and D&C Yellow No. 10 for the 75 mg strength.

CLINICAL PHARMACOLOGY

Tetracyclines are readily absorbed and are bound to plasma proteins in varying degrees. They are concentrated by the liver in the bile and excreted in the urine and feces at high concentrations in a biologically active form. Doxycycline is virtually completely absorbed after oral administration.

Following a 200 mg dose of doxycycline monohydrate, 24 normal adult volunteers averaged the following serum concentration values:

Time (hr): | 0.5 | 1.0 | 1.5 | 2.0 | 3.0 | 4.0 | 8.0 | 12.0 | 24.0 | 48.0 | 72.0
Conc. | 1.02 | 2.26 | 2.67 | 3.01 | 3.16 | 3.03 | 2.03 | 1.62 | 0.95 | 0.37 | 0.15 | (μg/mL)

Average Observed Values
Maximum Concentration | 3.61 μg/mL (± 0.9 sd)
Time of Maximum Concentration | 2.60 hr (± 1.10 sd)
Elimination Rate Constant | 0.049 per hr (± 0.030 sd)
Half-Life | 16.33 hr (± 4.53 sd)

Excretion of doxycycline by the kidney is about 40%/72 hours in individuals with normal function (creatinine clearance about 75 mL/min). This percentage excretion may fall as low as 1-5%/72 hours in individuals with severe renal insufficiency (creatinine clearance below 10 mL/min). Studies have shown no significant difference in serum half-life of doxycycline (range 18-22 hours) in individuals with normal and severely impaired renal function.

Hemodialysis does not alter serum half-life.

Microbiology: The tetracyclines are primarily bacteriostatic and are thought to exert their antimicrobial effect by the inhibition of protein synthesis. The tetracyclines, including doxycycline, have a similar antimicrobial spectrum of activity against a wide range of gram-positive and gram-negative microorganisms. Cross-resistance of these microorganisms to tetracyclines is common.

Doxycycline has been shown to be active against most strains of the following microorganisms, both in vitro and in clinical infections as described in the INDICATIONS AND USAGE section.

Aerobic Gram-Positive Microorganisms:

Because many strains of the following groups of gram-positive microorganisms have been shown to be resistant to tetracyclines, culture and susceptibility testing are recommended.

Bacillus anthracis
Listeria monocytogenes
Staphylococcus aureus*

*Doxycycline is not the drug of choice in the treatment of any type of staphylococcal infection.

Up to 44 percent of strains of Streptococcus pyogenes and 74 percent of Streptococcus faecalis have been found to be resistant to tetracycline drugs. Therefore, tetracyclines should not be used to treat streptococcal infections unless the microorganism has been demonstrated to be susceptible.

Streptococcus pneumoniae

Aerobic Gram-Negative Microorganisms:

Bartonella bacilliformis | Haemophilus ducreyi
Brucella species | Haemophilus influenzae
Calymmatobacterium granulomatis | Neisseria gonorrhoeae
Campylobacter fetus | Vibrio cholerae
Francisella tularensis | Yersinia pestis

Because many strains of the following groups of gram-negative microorganisms have been shown to be resistant to tetracyclines, culture and susceptibility testing are recommended:

Acinetobacter species | Klebsiella species
Enterobacter aerogenes | Shigella species
Escherichia coli

Anaerobic Microorganisms:

Actinomyces israelii | Fusobacterium fusiforme
Clostridium species

Other Microorganisms:

Borrelia recurrentis | Rickettsiae
Chlamydia psittaci | Treponema pallidum
Chlamydia trachomatis | Treponema pertenue
Mycoplasma pneumoniae

Susceptibility Tests:

Dilution Techniques:

Quantitative methods are used to determine antimicrobial minimum inhibitory concentrations (MIC’s). These MIC’s provide estimates of the susceptibility of bacteria to antimicrobial compounds. The MIC’s should be determined using a standardized procedure. Standardized procedures are based on a dilution method^1,3 (broth or agar) or equivalent with standardized inoculum concentrations and standardized concentrations of tetracycline powder. The MIC values should be interpreted according to the following criteria:

Interpretive criteria for Enterobacteriaceae, Staphylococcus aureus and Acinetobacter spp.
Microorganism | MIC Interpretive Standard (μg/mL)
Microorganism | Susceptible (S) | Intermediate (I) | Resistant (R)
Enterobacteriaceae | ≤ 4 | 8 | ≥ 16
Staphylococcus aureus | ≤ 4 | 8 | ≥ 16
Acinetobacter spp. | ≤ 4 | 8 | ≥ 16

Microorganisms that are susceptible to tetracycline are generally susceptible to doxycycline.

Interpretive Criteria for Haemophilus spp.
Microorganism | MIC Interpretive Standard (μg/mL)
Microorganism | Susceptible (S) | Intermediate (I) | Resistant (R)
Haemophilus spp. | ≤ 2 | 4 | ≥ 8

Interpretive criteria for Haemophilus spp. are applicable only to tests performed by broth microdilution method using Haemophilus Test Medium (HTM).^1,3
Microorganisms that are susceptible to tetracycline are generally susceptible to doxycycline.

Interpretive Criteria for Neisseria gonorrhoeae
Microorganism | MIC Interpretive Standard (μg/mL)
Microorganism | Susceptible (S) | Intermediate (I) | Resistant (R)
Neisseria gonorrhoeae | ≤ 0.25 | 0.5 - 1 | ≥ 2

Interpretive criteria for Neisseria gonorrhoeae are applicable only to tests performed by agar dilution method using GC agar base with 1% defined growth supplement.^1,3
Microorganisms that are susceptible to tetracycline are generally susceptible to doxycycline.

Interpretive Criteria for Streptococcus pneumoniae
Microorganism | MIC Interpretive Standard (μg/mL)
Microorganism | Susceptible (S) | Intermediate (I) | Resistant (R)
Streptococcus pneumoniae | ≤ 2 | 4 | ≥ 8

Interpretive criteria for Streptococcus pneumoniae are applicable only to tests performed by broth microdilution method using Cation-Adjusted Mueller-Hinton broth with 2.5% - 5% lysed horse blood.^1,3
Microoganisms that are susceptible to tetracycline are generally susceptible to doxycycline.

Interpretive Criteria for Bacillus anthracis and Brucella spp.
Microorganism | MIC Interpretive Standard (μg/mL)
Microorganism | Susceptible (S) | Intermediate (I) | Resistant (R)
Bacillus anthracis | ≤ 1 | - | -
Brucella spp. | ≤ 1 | - | -

Broth Microdilution performed in unsupplemented Brucella broth pH adjusted to 7.1 ± 0.1 for Brucella spp.^5
For some organism/antimicrobial agent combinations, the absence or rare occurrence of resistant strains precludes defining results for categories other than “susceptible.” For strains yielding results suggestive of a “nonsusceptible” category, organism identification and antimicrobial susceptibility test results should be confirmed.^5

Incubation in 5% CO2 may be required for growth of some strains of Brucella spp. especially B. abortus.
Incubation broth MIC tests in CO2 may decrease the MIC of tetracyclines, usually by one doubling dilution.^5
Microorganisms that are susceptible to tetracycline are generally susceptible to doxycycline.

Interpretive Criteria for Burkholderia mallei, Burkholderia pseudomallei and Yersinia pestis
Microorganism | MIC Interpretive Standard (μg/mL)
Microorganism | Susceptible (S) | Intermediate (I) | Resistant (R)
Burkholderia mallei | ≤ 4 | 8 | ≥ 16
Burkholderia pseudomallei | ≤ 4 | 8 | ≥ 16
Yersinia pestis | ≤ 4 | 8 | ≥ 16

Microorganisms that are susceptible to tetracycline are generally susceptible to doxycycline.

Interpretive Criteria for Franciscella tularensis
Microorganism | MIC Interpretive Standard (μg/mL)
Microorganism | Susceptible (S) | Intermediate (I) | Resistant (R)
Franciscella tularensis | ≤ 4 | - | -

Broth Microdilutions performed in Cation-Adjusted Mueller-Hinton broth with 2% defined growth supplement for Franciscella tularensis^5

For some organism/antimicrobial agent combinations, the absence or rare occurrence of resistant strains precludes defining results for categories other than “susceptible.” For strains yielding results suggestive of a “nonsusceptible” category, organism identification and antimicrobial susceptibility test results should be confirmed.^5

Microorganisms that are susceptible to tetracycline are generally susceptible to doxycycline.

A report of “Susceptible” indicates that the pathogen is likely to be inhibited if the antimicrobial compound in the blood reaches the concentrations usually achievable. A report of “Intermediate” indicates that the result should be considered equivocal, and, if the microorganism is not fully susceptible to alternative, clinically feasible drugs, the test should be repeated. This category implies possible clinical applicability in body sites where the drug is physiologically concentrated or in situations where high dosage of drug can be used. This category also provides a buffer zone which prevents small uncontrolled technical factors from causing major discrepancies in interpretation. A report of “Resistant” indicates that the pathogen is not likely to be inhibited if the antimicrobial compound in the blood reaches the concentrations usually achievable; other therapy should be selected.

Standardized susceptibility test procedures require the use of laboratory control microorganisms to control the technical aspects of the laboratory procedures. Standard tetracycline powder should provide the following MIC values:

Quality Control Ranges for MIC Broth Dilution Method
Microorganism | ATCC Number | Cation-Adjusted Mueller-Hinton (CAMHB) MIC (μg/mL)
Escherichia coli | 25922 | 0.5 - 2
Haemophilus influenzae | 49247 | 4 - 32
Neisseria gonorrhoeae | 49226 | 0.25 - 1
Pseudomonas aeruginosa | 27853 | 8 - 32
Staphylococcus aureus | 29213 | 0.12 - 1
Streptococcus pneumoniae | 49619 | 0.06 - 0.5

Diffusion Techniques:

Quantitative methods that require measurement of zone diameters also provide reproducible estimates of the susceptibility of bacteria to antimicrobial compounds. One such standardized procedure^2,3 requires the use of standardized inoculum concentrations. This procedure uses paper disks impregnated with 30-μg tetracycline or 30-μg doxycycline to test the susceptibility of microorganisms to doxycycline.

Reports from the laboratory providing results of the standard single-disk susceptibility test with a 30-μg tetracycline-class disk or the 30-μg doxycycline disk should be interpreted according to the following criteria:

Interpretive Zone Diameters for Staphylococcus aureus
Antimicrobial Agent | Zone Diameter (nearest whole mm)
Antimicrobial Agent | Susceptible (S) | Intermediate (I) | Resistant (R)
Tetracycline | ≥ 19 | 15 - 18 | ≤ 14
Doxycycline | ≥ 16 | 13 - 15 | ≤ 12

Interpretive Zone Diameters for Enterobacteriaceae.
Antimicrobial Agent | Zone Diameter (nearest whole mm)
Antimicrobial Agent | Susceptible (S) | Intermediate (I) | Resistant (R)
Tetracycline | ≥ 15 | 12 - 14 | ≤ 11
Doxycycline | ≥ 14 | 11 - 13 | ≤ 10
Minocycline | ≥ 16 | 13 - 15 | ≤ 12

Interpretive Zone Diameters for Acinetobactor spp.
Antimicrobial Agent | Zone Diameter (nearest whole mm)
Antimicrobial Agent | Susceptible (S) | Intermediate (I) | Resistant (R)
Tetracycline | ≥ 15 | 12 - 14 | ≤ 11
Doxycycline | ≥ 13 | 10 - 12 | ≤ 9
Minocycline | ≥ 16 | 13 - 15 | ≤ 12

Interpretive Zone Diameters for Haemophilus spp.
Antimicrobial Agent | Zone Diameter (nearest whole mm)
Antimicrobial Agent | Susceptible (S) | Intermediate (I) | Resistant (R)
Tetracycline | ≥ 29 | 26 - 28 | ≤ 25

Interpretive criteria applicable only to tests performed by disk diffusion method using a 30-μg tetracycline-class disk and using Haemophilus Test Medium (HTM).^2,3
Microorganisms that are susceptible to tetracycline are generally susceptible to doxycycline.

Interpretive Zone Diameters for Neisseria gonorrhoeae
Antimicrobial Agent | Zone Diameter (nearest whole mm)
Antimicrobial Agent | Susceptible (S) | Intermediate (I) | Resistant (R)
Tetracycline | ≥ 38 | 31 - 37 | ≤ 30

Interpretive criteria applicable only to tests performed by disk diffusion method using a 30-μg tetracycline-class disk and using GC agar base with 1% defined growth supplement.^2,3
Zone diameters ≤ 19 mm may indicate a plasmid-mediated tetracycline-resistant Neisseria gonorrhoeae (TRNG) isolate. These TRNG strains should be confirmed by the dilution test (MIC ≥ 16 μg/mL).
Microorganisms that are susceptible to tetracycline are generally susceptible to doxycycline.

Interpretive Zone Diameters for Streptococcus pneumoniae
Antimicrobial Agent | Zone Diameter (nearest whole mm)
Antimicrobial Agent | Susceptible (S) | Intermediate (I) | Resistant (R)
Tetracycline | ≥ 23 | 19 - 22 | ≤ 18

Interpretative criteria applicable only to tests performed by disk diffusion method using a 30-μg tetracycline-class disk and using Mueller-Hinton agar with 5% defibrinated sheep blood and incubated in 5% CO2.^2,3
Microorganisms that are susceptible to tetracycline are generally susceptible to doxycycline.

Interpretation should be as stated above for results using dilution techniques. Interpretation involves correlation of the diameter obtained in the disk test with the MIC for tetracycline or doxycycline, respectively.

As with standardized dilution techniques, diffusion methods require the use of laboratory control microorganisms that are used to control the technical aspects of the laboratory procedures. For the diffusion technique, the 30-μg tetracycline-class disk or the 30-μg doxycycline disk should provide the following zone diameters in these laboratory test quality control strains:

Quality Control Zone Diameters for Disk Diffusion Method
Microorganism | ATCC Number | Zone Diameter (mm)
Microorganism | ATCC Number | Tetracycline |  | Doxycycline |  | Minocycline
Escherichia coli | 25922 | 18 - 25 |  | 18 - 24 |  | 19 - 25
Haemophilus influenzae | 49247 | 14 - 22 |  | - |  | -
Neisseria gonorrhoeae | 49226 | 30 - 42 |  | - |  | -
Staphylococcus aureus | 25923 | 24 - 30 |  | 23 - 29 |  | 25 - 30
Streptococcus pneumoniae | 49619 | 27 - 31 |  | - |  | -

Anaerobic Techniques:

For anaerobic bacteria, the susceptibility to tetracycline as MIC’s can be determined by standardized test methods.^3,4 The MIC values obtained should be interpreted according to the following criteria:

Agar Dilution Interpretive Criteria for Anaerobes
Microorganism | MIC Interpretive Standard (μg/mL)
Microorganism | Susceptible (S) | Intermediate (I) | Resistant (R)
Anaerobes | ≤ 4 | 8 | ≥ 16

Microorganisms that are susceptible to tetracycline are generally susceptible to doxycycline.
Interpretation is identical to that stated above for results using dilution techniques.

As with other susceptibility techniques, the use of laboratory control microorganisms is required to control the technical aspects of the laboratory standardized procedures. Standardized tetracycline powder should provide the following MIC values:

Quality Control Ranges for MIC Agar Dilution Method
Microorganism | ATCC Number | MIC (μg/mL)
Bacteroides fragilis | 25285 | 0.125 - 0.5
Bacteroides thetaiotamicron | 29741 | 8 - 32

Range applicable only to tests performed by the reference agar dilution method.

INDICATIONS AND USAGE

To reduce the development of drug-resistant bacteria and maintain effectiveness of Doxycycline Monohydrate Capsules and other antibacterial drugs, Doxycycline Monohydrate Capsules should be used only to treat or prevent infections that are proven or strongly suspected to be caused by susceptible bacteria. When culture and susceptibility information are available, they should be considered in selecting or modifying antibacterial therapy. In the absence of such data, local epidemiology and susceptibility patterns may contribute to the empiric selection of therapy.

Doxycycline is indicated for the treatment of the following infections:
Rocky mountain spotted fever, typhus fever and the typhus group, Q fever, rickettsialpox, and tick fevers caused by Rickettsiae.
Respiratory tract infections caused by Mycoplasma pneumoniae.
Lymphogranuloma venereum caused by Chlamydia trachomatis.
Psittacosis (ornithosis) caused by Chlamydia psittaci.
Trachoma caused by Chlamydia trachomatis, although the infectious agent is not always eliminated as judged by immunofluorescence.
Inclusion conjunctivitis caused by Chlamydia trachomatis.
Uncomplicated urethral, endocervical or rectal infections in adults caused by Chlamydia trachomatis.
Nongonococcal urethritis caused by Ureaplasma urealyticum.
Relapsing fever due to Borrelia recurrentis.

Doxycycline is also indicated for the treatment of infections caused by the following gram-negative microorganisms:
Chancroid caused by Haemophilus ducreyi.
Plague due to Yersinia pestis (formerly Pasteurella pestis).
Tularemia due to Francisella tularensis (formerly Pasteurella tularensis).
Cholera caused by Vibrio cholerae (formerly Vibrio comma).
Campylobacter fetus infections caused by Campylobacter fetus (formerly Vibrio fetus).
Brucellosis due to Brucella species (in conjunction with streptomycin).
Bartonellosis due to Bartonella bacilliformis.
Granuloma inguinale caused by Calymmatobacterium granulomatis.

Because many strains of the following groups of microorganisms have been shown to be resistant to doxycycline, culture and susceptibility testing are recommended.

Doxycycline is indicated for treatment of infections caused by the following gram-negative microorganisms, when bacteriologic testing indicates appropriate susceptibility to the drug:
Escherichia coli
Enterobacter aerogenes (formerly Aerobacter aerogenes)
Shigella species
Acinetobacter species (formerly Mima species and Herellea species)
Respiratory tract infections caused by Haemophilus influenzae.
Respiratory tract and urinary tract infections caused by Klebsiella species.

Doxycycline is indicated for treatment of infections caused by the following gram-positive microorganisms when bacteriologic testing indicates appropriate susceptibility to the drug:
Upper respiratory infections caused by Streptococcus pneumoniae (formerly Diplococcus pneumoniae).
Skin and skin structure infections caused by Staphylococcus aureus.
Anthrax due to Bacillus anthracis, including inhalational anthrax (post-exposure): to reduce the incidence or progression of disease following exposure to aerosolized Bacillus anthracis.

Doxycycline is not the drug of choice in the treatment of any type of staphylococcal infections.

When penicillin is contraindicated, doxycycline is an alternative drug in the treatment of the following infections:
Uncomplicated gonorrhea caused by Neisseria gonorrhoeae.
Syphilis caused by Treponema pallidum.
Yaws caused by Treponema pertenue.
Listeriosis due to Listeria monocytogenes.
Vincent’s infection caused by Fusobacterium fusiforme.
Actinomycosis caused by Actinomyces israelii.
Infections caused by Clostridium species.

In acute intestinal amebiasis, doxycycline may be a useful adjunct to amebicides.

In severe acne, doxycycline may be useful adjunctive therapy.

CONTRAINDICATIONS

This drug is contraindicated in persons who have shown hypersensitivity to any of the tetracyclines.

WARNINGS

THE USE OF DRUGS OF THE TETRACYCLINE CLASS DURING TOOTH DEVELOPMENT (LAST HALF OF PREGNANCY, INFANCY, AND CHILDHOOD TO THE AGE OF 8 YEARS) MAY CAUSE PERMANENT DISCOLORATION OF THE TEETH (YELLOW-GRAY-BROWN). This adverse reaction is more common during long-term use of the drugs but has been observed following repeated short-term courses. Enamel hypoplasia has also been reported. TETRACYCLINE DRUGS, THEREFORE, SHOULD NOT BE USED IN THIS AGE GROUP, EXCEPT FOR ANTHRAX, INCLUDING INHALATIONAL ANTHRAX (POST-EXPOSURE), UNLESS OTHER DRUGS ARE NOT LIKELY TO BE EFFECTIVE OR ARE CONTRAINDICATED.

Clostridium difficile associated diarrhea (CDAD) has been reported with use of nearly all antibacterial agents, including Doxycycline Monohydrate Capsules, and may range in severity from mild diarrhea to fatal colitis. Treatment with antibacterial agents alters the normal flora of the colon leading to overgrowth of C. difficile.

C. difficile produces toxins A and B which contribute to the development of CDAD. Hypertoxin producing strains of C. difficile cause increased morbidity and mortality, as these infections can be refractory to antimicrobial therapy and may require colectomy. CDAD must be considered in all patients who present with diarrhea following antibiotic use. Careful medical history is necessary since CDAD has been reported to occur over two months after the administration of antibacterial agents.

If CDAD is suspected or confirmed, ongoing antibiotic use not directed against C. difficile may need to be discontinued. Appropriate fluid and electrolyte management, protein supplementation, antibiotic treatment of C. difficile, and surgical evaluation should be instituted as clinically indicated.

All tetracyclines form a stable calcium complex in any bone-forming tissue. A decrease in the fibula growth rate has been observed in prematures given oral tetracycline in doses of 25 mg/kg every six hours. This reaction was shown to be reversible when the drug was discontinued.

Results of animal studies indicate that tetracyclines cross the placenta, are found in fetal tissues, and can have toxic effects on the developing fetus (often related to retardation of skeletal development). Evidence of embryo toxicity has been noted in animals treated early in pregnancy. If any tetracycline is used during pregnancy or if the patient becomes pregnant while taking these drugs, the patient should be apprised of the potential hazard to the fetus.

The antianabolic action of the tetracyclines may cause an increase in BUN. Studies to date indicate that this does not occur with the use of doxycycline in patients with impaired renal function.

Photosensitivity manifested by an exaggerated sunburn reaction has been observed in some individuals taking tetracyclines. Patients apt to be exposed to direct sunlight or ultraviolet light should be advised that this reaction can occur with tetracycline drugs, and treatment should be discontinued at the first evidence of skin erythema.

PRECAUTIONS

General:

As with other antibiotic preparations, use of this drug may result in overgrowth of non-susceptible organisms, including fungi. If superinfection occurs, the antibiotic should be discontinued and appropriate therapy instituted.

Bulging fontanels in infants and benign intracranial hypertension in adults have been reported in individuals receiving tetracyclines. These conditions disappeared when the drug was discontinued.

Incision and drainage or other surgical procedures should be performed in conjunction with antibiotic therapy when indicated.

Prescribing Doxycycline Monohydrate Capsules in the absence of proven or strongly suspected bacterial infection or a prophylactic indication is unlikely to provide benefit to the patient and increases the risk of the development of drug-resistant bacteria.

Information for Patients:

All patients taking doxycycline should be advised:

–to avoid excessive sunlight or artificial ultraviolet light while receiving doxycycline and to discontinue therapy if phototoxicity (e.g., skin eruptions, etc.) occurs. Sunscreen or sunblock should be considered. (See WARNINGS.)

–to drink fluids liberally along with doxycycline to reduce the risk of esophageal irritation and ulceration. (See ADVERSE REACTIONS.)

–that the absorption of tetracyclines is reduced when taken with foods, especially those which contain calcium. However, the absorption of doxycycline is not markedly influenced by simultaneous ingestion of food or milk. (See Drug Interactions.)

–that the absorption of tetracyclines is reduced when taking bismuth subsalicylate. (See Drug Interactions.)

–not to use outdated or poorly stored doxycycline.

–that the use of doxycycline might increase the incidence of vaginal candidiasis.

Diarrhea is a common problem caused by antibiotics which usually ends when the antibiotic is discontinued. Sometimes after starting treatment with antibiotics, patients can develop watery and bloody stools (with or without stomach cramps and fever) even as late as two or more months after having taken the last dose of the antibiotic. If this occurs, patients should contact their physician as soon as possible.

Patients should be counseled that antibacterial drugs including Doxycycline Monohydrate Capsules should only be used to treat bacterial infections. They do not treat viral infections (e.g., the common cold). When doxycycline monohydrate capsules are prescribed to treat a bacterial infection, patients should be told that although it is common to feel better early in the course of therapy, the medication should be taken exactly as directed. Skipping doses or not completing the full course of therapy may (1) decrease the effectiveness of the immediate treatment and (2) increase the likelihood that bacteria will develop resistance and will not be treatable by Doxycycline Monohydrate Capsules or other antibacterial drugs in the future.

Laboratory Tests:

In venereal disease when coexistent syphilis is suspected, a dark-field examination should be done before treatment is started and the blood serology repeated monthly for at least four months.

In long-term therapy, periodic laboratory evaluations of organ systems, including hematopoietic, renal, and hepatic studies should be performed.

Drug Interactions:

Because tetracyclines have been shown to depress plasma prothrombin activity, patients who are on anticoagulant therapy may require downward adjustment of their anticoagulant dosage.

Since bacteriostatic drugs may interfere with the bactericidal action of penicillin, it is advisable to avoid giving tetracyclines in conjunction with penicillin.

Absorption of tetracyclines is impaired by antacids containing aluminum, calcium, or magnesium, and iron-containing preparations.

Barbiturates, carbamazepine, and phenytoin decrease the half-life of doxycycline.

The concurrent use of tetracycline and methoxyflurane has been reported to result in fatal renal toxicity.

Concurrent use of tetracycline may render oral contraceptives less effective.

Drug/Laboratory Test Interactions:

False elevations of urinary catecholamine levels may occur due to interference with the fluorescence test.

Carcinogenesis, Mutagenesis, Impairment of Fertility:

Long-term studies in animals to evaluate the carcinogenic potential of doxycycline have not been conducted. However, there has been evidence of oncogenic activity in rats in studies with related antibiotics, oxytetracycline (adrenal and pituitary tumors) and minocycline (thyroid tumors). Likewise, although mutagenicity studies of doxycycline have not been conducted, positive results in in vitro mammalian cell assays have been reported for related antibiotics (tetracycline, oxytetracycline). Doxycycline administered orally at dosage levels as high as 250 mg/kg/day had no apparent effect on the fertility of female rats. Effect on male fertility has not been studied.

Pregnancy:

Teratogenic Effects.

Pregnancy Category D:

There are no adequate and well-controlled studies on the use of doxycycline in pregnant short-term, first trimester exposure. There are no human data available to assess the effects of long-term therapy of doxycycline in pregnant women such as that proposed for treatment of anthrax exposure. An expert review of published data on experiences with doxycycline use during pregnancy by TERIS - the Teratogen Information System - concluded that therapeutic doses during pregnancy are unlikely to pose a substantial teratogenic risk (the quantity and quality of data were assessed as limited to fair), but the data are insufficient to state that there is no risk.^6

A case-control study (18,515 mothers of infants with congenital anomalies and 32,804 mothers of infants with no congenital anomalies) shows a weak but marginally statistically significant association with total malformations and use of doxycycline anytime during pregnancy. (Sixty-three [0.19%] of the controls and 56 [0.30%] of the cases were treated with doxycycline.) This association was not seen when the analysis was confined to maternal treatment during the period of organogenesis (i.e., in the second and third months of gestation) with the exception of a marginal relationship with neural tube defect based on only two exposed cases.^7

A small prospective study of 81 pregnancies describes 43 pregnant women treated for 10 days with doxycycline during early first trimester. All mothers reported their exposed infants were normal at 1 year of age.^8

Labor and Delivery:

The effect of tetracyclines on labor and delivery is unknown.

Nursing Mothers:

Tetracyclines are excreted in human milk, however, the extent of absorption of tetracyclines, including doxycycline, by the breastfed infant is not known. Short-term use by lactating women is not necessarily contraindicated; however, the effects of prolonged exposure to doxycycline in breast milk are unknown.^9 Because of the potential for adverse reactions in nursing infants from doxycycline, a decision should be made whether to discontinue nursing or to discontinue the drug, taking into account the importance of the drug to the mother. (See WARNINGS.)

Pediatric Use:

See WARNINGS and DOSAGE AND ADMINISTRATION sections.

ADVERSE REACTIONS

Due to oral doxycycline’s virtually complete absorption, side effects to the lower bowel, particularly diarrhea, have been infrequent. The following adverse reactions have been observed in patients receiving tetracyclines.

Gastrointestinal: Anorexia, nausea, vomiting, diarrhea, glossitis, dysphagia, enterocolitis, and inflammatory lesions (with monilial overgrowth) in the anogenital region. Hepatotoxicity has been reported. These reactions have been caused by both the oral and parenteral administration of tetracyclines. Rare instances of esophagitis and esophageal ulcerations have been reported in patients receiving capsule and tablet forms of drugs in the tetracycline class. Most of these patients took medications immediately before going to bed. (See DOSAGE AND ADMINISTRATION.)

Skin: Maculopapular and erythematous rashes, Stevens-Johnson syndrome, toxic epidermal necrolysis, and erythema multiforme have been reported. Exfoliative dermatitis has been reported but is uncommon. Photosensitivity is discussed above. (See WARNINGS.)

Renal Toxicity: Rise in BUN has been reported and is apparently dose related. (See WARNINGS.)

Hypersensitivity Reactions: Urticaria, angioneurotic edema, anaphylaxis, anaphylactoid purpura, serum sickness, pericarditis, and exacerbation of systemic lupus erythematosus.

Blood: Hemolytic anemia, thrombocytopenia, neutropenia, and eosinophilia have been reported with tetracyclines.

Other: Bulging fontanels in infants and intracranial hypertension in adults. (See PRECAUTIONS-General.)

When given over prolonged periods, tetracyclines have been reported to produce brown-black microscopic discoloration of the thyroid gland. No abnormalities of thyroid function are known to occur.

OVERDOSAGE

In case of overdosage, discontinue medication, treat symptomatically and institute supportive measures. Dialysis does not alter serum half-life, and it would not be of benefit in treating cases of overdosage.

DOSAGE AND ADMINISTRATION

THE USUAL DOSAGE AND FREQUENCY OF ADMINISTRATION OF DOXYCYCLINE DIFFERS FROM THAT OF THE OTHER TETRACYCLINES. EXCEEDING THE RECOMMENDED DOSAGE MAY RESULT IN AN INCREASED INCIDENCE OF SIDE EFFECTS.

Adults: The usual dose of oral doxycycline is 200 mg on the first day of treatment (administered 100 mg every 12 hours or 50 mg every 6 hours) followed by a maintenance dose of 100 mg/day. The maintenance dose may be administered as a single dose or as 50 mg every 12 hours. In the management of more severe infections (particularly chronic infections of the urinary tract), 100 mg every 12 hours is recommended.

For pediatric patients above eight years of age: The recommended dosage schedule for pediatric patients weighing 100 pounds or less is 2 mg/lb of body weight divided into two doses on the first day of treatment, followed by 1 mg/lb of body weight given as a single daily dose or divided into two doses, on subsequent days. For more severe infections up to 2 mg/lb of body weight may be used. For pediatric patients over 100 pounds the usual adult dose should be used.

Uncomplicated gonococcal infections in adults (except anorectal infections in men): 100 mg, by mouth, twice a day for 7 days. As an alternate single visit dose, administer 300 mg stat followed in one hour by a second 300 mg dose.

Acute epididymo-orchitis caused by N. gonorrhoeae: 100 mg, by mouth, twice a day for at least 10 days.

Primary and secondary syphilis: 300 mg a day in divided doses for at least 10 days.

Uncomplicated urethral, endocervical, or rectal infection in adults caused by Chlamydia trachomatis: 100 mg, by mouth, twice a day for at least 7 days.

Nongonococcal urethritis caused by C. trachomatis and U. urealyticum: 100 mg, by mouth, twice a day for at least 7 days.

Acute epididymo-orchitis caused by C. trachomatis: 100 mg, by mouth, twice a day for at least 10 days.

Inhalational anthrax (post-exposure): ADULTS: 100 mg of doxycycline, by mouth, twice a day for 60 days. CHILDREN: weighing less than 100 pounds (45 kg); 1 mg/lb (2.2 mg/kg) of body weight, by mouth, twice a day for 60 days. Children weighing 100 pounds or more should receive the adult dose.

When used in streptococcal infections, therapy should be continued for 10 days.

Administration of adequate amounts of fluid along with capsule and tablet forms of drugs in the tetracycline class is recommended to wash down the drugs and reduce the risk of esophageal irritation and ulceration. (See ADVERSE REACTIONS.) If gastric irritation occurs, doxycycline may be given with food. Ingestion of a high fat meal has been shown to delay the time to peak plasma concentrations by an average of one hour and 20 minutes. However, in the same study, food enhanced the average peak concentration by 7.5% and the area under the curve by 5.7%.

HOW SUPPLIED

Doxycycline Monohydrate Capsules 100 mg have an ivory opaque body with a brown opaque cap. The capsule bears the inscription WATSON 411 in white and 100 mg in brown. Each capsule contains doxycycline monohydrate equivalent to 100 mg of doxycycline, supplied in

Bottles of 30 | NDC 54868-6190-0

Store at 20° - 25°C (68° -77°F). [See USP controlled room temperature.]
Dispense in a tight light-resistant container as defined in the USP/NF.

ANIMAL PHARMACOLOGY AND ANIMAL TOXICOLOGY

Hyperpigmentation of the thyroid has been produced by members of the tetracycline class in the following species: in rats by oxytetracycline, doxycycline, tetracycline PO4, and methacycline; in minipigs by doxycycline, minocycline, tetracycline PO4, and methacycline; in dogs by doxycycline and minocycline; in monkeys by minocycline.

Minocycline, tetracycline PO4, methacycline, doxycycline, tetracycline base, oxytetracycline HCl and tetracycline HCl were goitrogenic in rats fed a low iodine diet. This goitrogenic effect was accompanied by high radioactive iodine uptake. Administration of minocycline also produced a large goiter with high radioiodine uptake in rats fed a relatively high iodine diet.

Treatment of various animal species with this class of drugs has also resulted in the induction of thyroid hyperplasia in the following: in rats and dogs (minocycline), in chickens (chlortetracycline) and in rats and mice (oxytetracycline). Adrenal gland hyperplasia has been observed in goats and rats treated with oxytetracycline.

REFERENCES

1. Clinical and Laboratory Standards Institute. Methods for Dilution Antimicrobial Susceptibility Tests for Bacteria that Grow Aerobically – Seventh Edition. Approved Standard CLSI Document M07-A8, Vol. 29, No. 2, CLSI, Wayne, PA, January, 2009.
2. Clinical and Laboratory Standards Institute. Performance Standards for Antimicrobial Disk Susceptibility Tests – Ninth Edition. Approved Standard CLSI Document M02-A10, Vol. 29, No. 1, CLSI, Wayne, PA, January, 2009.
3. Clinical and Laboratory Standards Institute. Performance Standards for Antimicrobial Susceptibility Testing – Twenty-First Informational Supplement. CLSI Document M100-S21, Vol. 31, No. 1, CLSI, Wayne, PA, January, 2011.
4. Clinical and Laboratory Standards Institute. Methods for Antimicrobial Susceptibility Testing of Anaerobic Bacteria – Seventh Edition. Approved Standard CLSI Document M11-A7, Vol. 27, No. 2, CLSI, Wayne, PA, December 2007.
5. Clinical and Laboratory Standards Institute. Methods for Antimicrobial Dilution and Disk Susceptibility Testing of Infrequently Isolated or Fastidious Bacteria: Approved Guidelines - 2nd Edition. CLSI Document M45-A2. CLSI, Wayne, PA, 2011
6. Friedman JM and Polifka JE. Teratogenic Effects of Drugs. A Resource for Clinicians (TERIS). Baltimore, MD: The Johns Hopkins University Press: 2000: 149-195.
7. Cziezel AE and Rockenbauer M. Teratogenic study of doxycycline. Obstet Gynecol 1997;89:524-528.
8. Horne HW Jr. and Kundsin RB. The role of mycoplasma among 81 consecutive pregnancies: a prospective study. Int J Fertil 1980; 25:315-317.
9. Hale T. Medications and Mothers Milk. 9th edition. Amarillo, TX: Pharmasoft Publishing 2000; 225-226.

Rx only

For all medical inquiries contact:
WATSON
Medical Communications
Parsippany, NJ 07054
800-272-5525

Distributed By:
Watson Pharma, Inc.
Parsippany, NJ 07054 USA

Revised: January 2012
191157-4

Relabeling and Repackaging by:
Physicians Total Care, Inc.
Tulsa, Oklahoma 74146

PRINCIPAL DISPLAY PANEL

Doxycycline Monohydrate Capsules
100 mg capsules